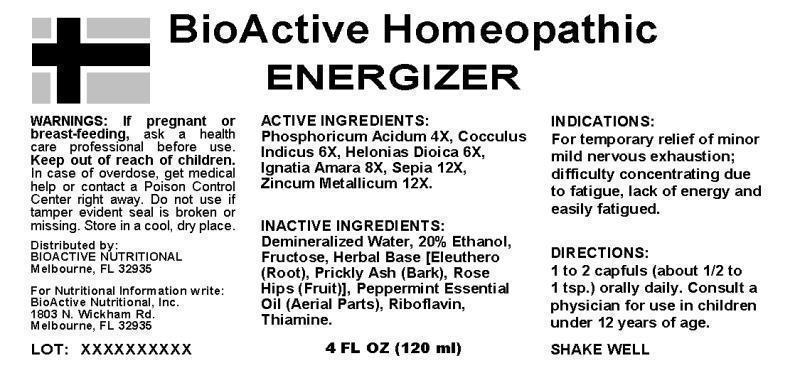 DRUG LABEL: ENERGIZER
NDC: 43857-0346 | Form: LIQUID
Manufacturer: BioActive Nutritional, Inc.
Category: homeopathic | Type: HUMAN OTC DRUG LABEL
Date: 20241017

ACTIVE INGREDIENTS: PHOSPHORIC ACID 4 [hp_X]/1 mL; ANAMIRTA COCCULUS SEED 6 [hp_X]/1 mL; CHAMAELIRIUM LUTEUM ROOT 6 [hp_X]/1 mL; STRYCHNOS IGNATII SEED 8 [hp_X]/1 mL; SEPIA OFFICINALIS JUICE 12 [hp_X]/1 mL; ZINC 12 [hp_X]/1 mL
INACTIVE INGREDIENTS: ELEUTHERO; ZANTHOXYLUM ZANTHOXYLOIDES BARK; ROSA CANINA FRUIT; FRUCTOSE; THIAMINE MONONITRATE; RIBOFLAVIN; PEPPERMINT OIL; WATER; ALCOHOL

DRUG FACTS:

ACTIVE INGREDIENTS:

PHOSPHORICUM ACIDUM 4X, COCCULUS INDICUS 6X, HELONIAS DIOICA 6X, IGNATIA AMARA 8X, SEPIA 12X, ZINCUM METALLICUM 12X

INDICATIONS:

For temporary relief of minor mild nervous exhaustion; difficulty concentrating due to fatigue, lack of energy and easily fatigued.

WARNINGS:

If pregnant or breast-feeding, ask a health care professional before use.

Keep out of reach of children. In case of overdose, get medical help or contact a Poison Control Center right away.

Do not use if tamper evident seal is broken or missing.

Store in a cool, dry place.

Keep out of reach of children. In case of overdose, get medical help or contact a Poison Control Center right away.

DIRECTIONS:

1 to 2 capfuls (about 1/2 to 1 tsp.) orally daily. Consult a physician for use in children under 12 years of age.

SHAKE WELL

INDICATIONS:

For temporary relief of minor mild nervous exhaustion; difficulty concentrating due to fatigue, lack of energy and easily fatigued.

INACTIVE INGREDIENTS:

ELEUTHEROCOCCUS SENTICOSUS (ROOT), ZANTHOXYLUM AMERICANUM (BARK), ROSA CANINA (FRUIT), FRUCTOSE (KRYSTAR 300), THIAMINE MONONITRATE, RIBOFLAVIN, MENTHA PIPERITA (AERIAL PARTS)

QUESTIONS:

Distributed by:

BIOACTIVE NUTRITIONAL

Melbourne, FL 32935

For Nutritional Information write:

BioActive Nutritional, Inc.

1803 N. Wickham Rd.

Melbourne, FL 32935

PACKAGE LABEL DISPLAY:

BioActive Homeopathic

ENERGIZER

4 FL OZ (120 ml)